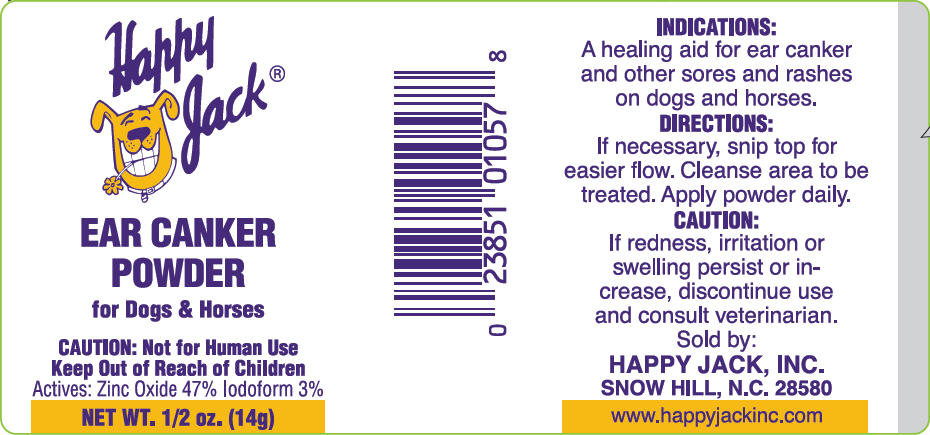 DRUG LABEL: Happy Jack Ear Canker
NDC: 23851-057 | Form: POWDER
Manufacturer: Happy Jack Inc
Category: animal | Type: OTC ANIMAL DRUG LABEL
Date: 20240801

ACTIVE INGREDIENTS: zinc oxide 470 mg/1 g; iodoform 30 mg/1 g
INACTIVE INGREDIENTS: talc; calcium carbonate

Happy Jack® Ear Canker Powder

INDICATIONS

A healing aid for ear canker and other sores and rashes on dogs and horses.

DIRECTIONS

If necessary, snip top for easier flow. Cleanse area to be treated. Apply powder daily.

CAUTION

If redness, irritation or swelling persist or increase, discontinue use and consult veterinarian.

Sold by:
HAPPY JACK, INC.
SNOW HILL, N.C. 28580

www.happyjackinc.com

PRINCIPAL DISPLAY PANEL - 14g Bottle Label

Happy Jack

EAR CANKER
POWDER
for Dogs & Horses

CAUTION: Not for Human Use
Keep Out of Reach of Children
Actives: Zinc Oxide 47% Iodoform 3%
NET WT. ½ oz. (14g)